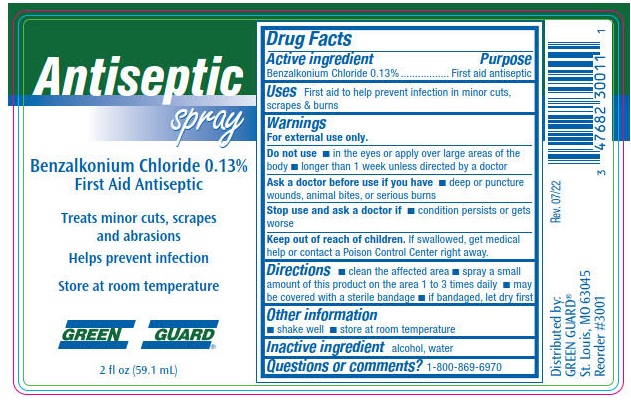 DRUG LABEL: Antiseptic
NDC: 47682-316 | Form: LIQUID
Manufacturer: Unifirst First Aid Corporation
Category: otc | Type: HUMAN OTC DRUG LABEL
Date: 20250908

ACTIVE INGREDIENTS: BENZALKONIUM CHLORIDE 1.3 g/1 L
INACTIVE INGREDIENTS: ALCOHOL; WATER

Green Guard Antiseptic Spray

Drug Facts

Active ingredients

Benzalkonium Chloride 0.13%

Purpose

First aid antiseptic

Uses

First aid to help prevent infection in minor cuts, scrapes and burns.

Warnings

For external use only.

Do not use

- in the eyes or apply over large areas of the body
- longer than one week unless directed by a doctor

Ask a doctor before use if you have

- deep or puncture wounds, animal bites, or serious burns

Stop use and ask a doctor if

- condition persists or gets worse

Keep out of reach of children. If swallowed, get medical help or contact a Poison Control Center right away.

Directions

- clean affected area
- spray a small amount of this product on the area1 to 3 times daily
- may be covered with a sterile bandage
- if bandaged, let dry first

Other information

- shake well
- store at room temperature

Inactive ingredients

alcohol, water

Questions or comments? 1-800-869-6970

Green Guard Antiseptic Spray Label

Antiseptic spray

Benzalkonium Chloride 0.13%

First Aid Antiseptic

Treats minor cuts, scrapes and abrasions

Helps prevent infection

Store at room temperature

GREEN GUARD ®

2 fl oz (59.1 mL)